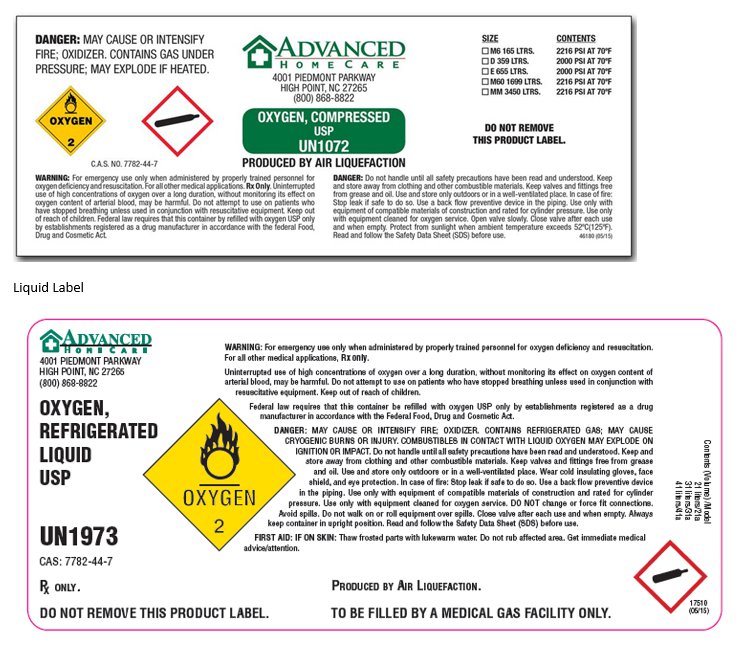 DRUG LABEL: Oxygen
NDC: 55813-123 | Form: GAS
Manufacturer: Advanced Home Care
Category: prescription | Type: HUMAN PRESCRIPTION DRUG LABEL
Date: 20151104

ACTIVE INGREDIENTS: OXYGEN 99 L/100 L

Oxygen, USP